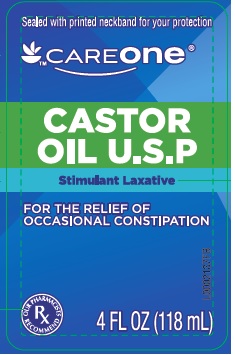 DRUG LABEL: Castor Oil
NDC: 72476-017 | Form: LIQUID
Manufacturer: Retail Business Services, LLC 
Category: otc | Type: HUMAN OTC DRUG LABEL
Date: 20260206

ACTIVE INGREDIENTS: CASTOR OIL 1 g/1 mL

Care One 078.000/078AA
Castor Oil

Active ingredient

Castor Oil USP 100%

Purpose

Stimulant laxative

Use

For relief of occasional constipation (iregularity). Generally produces bowel movement in 6 to 12 hours

Warnings

for this product

Do not use

For a period longer than 1 week

Ask a doctore before use if you have

- abdominal pain, nausea, or vomiting
- noticed a sudden change in bowel habits that persists over a period of 2 weeks

Ask a doctor or pharmacist before use

If you are taking any other drug. Take this product 2 or more hours before or after other drugs. Laxatives may affect how other drugs work.

Stop use and ask a doctor

If you have rectal bleeding or failure to have a bowel movement after use. These could be signs of a serious condition.

If pregnant or breast feeding

Ask a health professional before use.

Keep out of reach of children

In case of overdose, get medical help or contact a Poison Control Center right away

Directions

Adults and children over 12 years of age - 1 to a maximum of 4 Tablespoons (15 to 60 mL) in a single daily dose

children 2 to under 12 years of age - 1 to a maximum of 3 teaspoons (5 to 15 mL) in a single daily dose

children under 2 years of age - do not use, consult a doctor

Inactive Ingredient

NONE

other information

Keep tightly closed, away from excessive heat

DISTRIBUTED BY RETAIL BUSINESS SERVICES, LLC, LANDOVER, MD 20785

1-877-846-9949 2016 S&S Brands, LLC Quality guaranteed or your money back

principal display panel

Sealed with printed neckband for your protection

CAREONE CASTOR OIL U.S.P.

Stimulant Laxative

FOR THE RELIEF OF OCCASIONAL CONSTIPATION

OUR PHARMACISTS RECOMMENDED

4 FL OZ (118 mL)